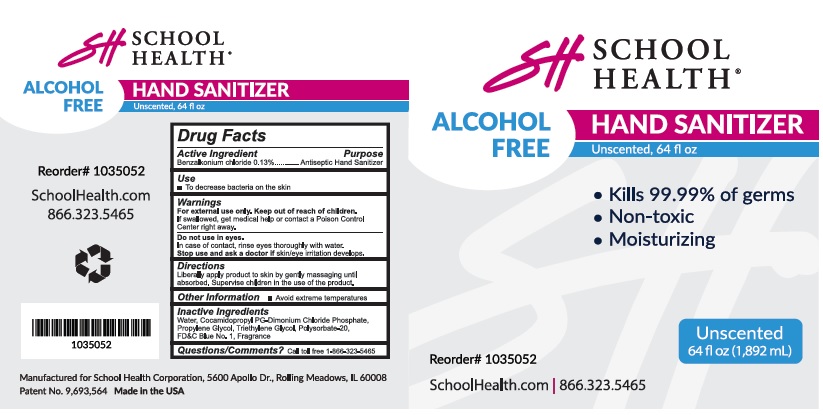 DRUG LABEL: School Health Hand Sanitizer
NDC: 76123-100 | Form: LIQUID
Manufacturer: School Health Corporation
Category: otc | Type: HUMAN OTC DRUG LABEL
Date: 20210524

ACTIVE INGREDIENTS: BENZALKONIUM CHLORIDE 0.13 g/100 mL
INACTIVE INGREDIENTS: WATER; COCAMIDOPROPYL PROPYLENE GLYCOL-DIMONIUM CHLORIDE PHOSPHATE; PROPYLENE GLYCOL; TRIETHYLENE GLYCOL; POLYSORBATE 20; FD&C BLUE NO. 1

School Health® Hand Sanitizer

Active Ingredient

Benzalkonium chloride 0.13%

Purpose

Antiseptic Hand Sanitizer

Use

- To decrease bacteria on the skin

Warnings

For external use only.

Keep out of reach of children.

If swallowed, get medical help or contact a Poison Control Center right away.

Do not use in eyes.

In case of contact, rinse eyes thoroughly with water.

Stop use and ask a doctor if

skin/eye irritation develops.

Directions

Liberally apply product to skin by gently massaging until absorbed. Supervise children in the use of the product.

Other Information

- Avoid extreme temperatures

Inactive Ingredients

Water, Cocamidolpropyl PG-Dimonium Chloride Phospate,

Propylene glycol, Triethylene glycol, Polysorbate-20,

FD&C Blue No. 1, Fragrance

Questions/Comments?

Call toll free 1-866-323-5465

Package Labeling

SCOOL HEALTH®
HAND SANITIZER

ALCOHOL FREE

HAND SANITIZER

Unscented, 64 fl oz

• Kills 99% of germs
• Non-toxic
• Moisturizing

Unscented
64 fl oz (1,892 mL)

ScoolHealth.com

866.323.5465

Manufactured for School Health Corporation, 56oo Apollo Dr., Rolling Meadows. IL 60008
Made in the USA

res